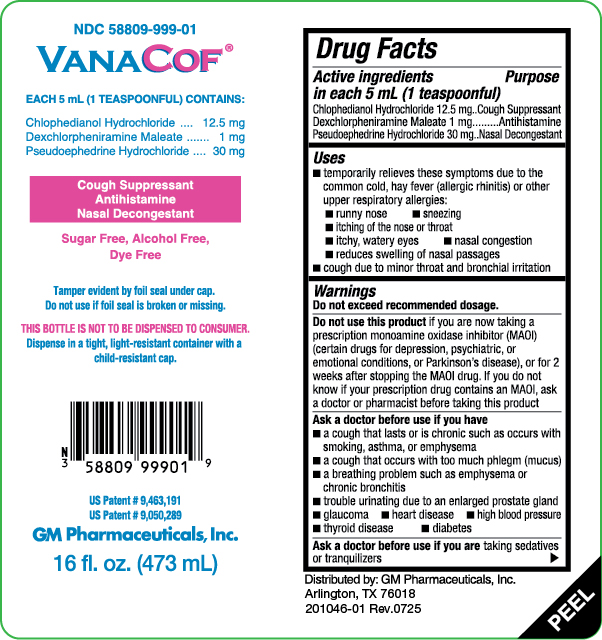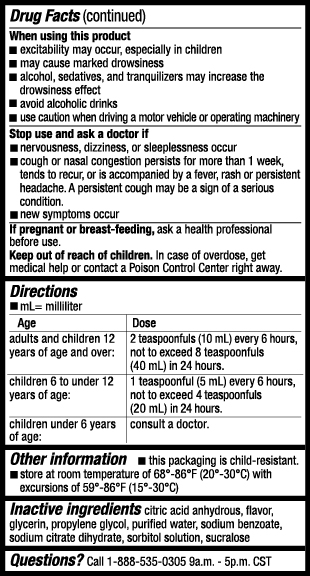 DRUG LABEL: VANACOF
NDC: 58809-999 | Form: LIQUID
Manufacturer: GM Pharmaceuticals, INC
Category: otc | Type: HUMAN OTC DRUG LABEL
Date: 20251014

ACTIVE INGREDIENTS: CHLOPHEDIANOL HYDROCHLORIDE 12.5 mg/5 mL; DEXCHLORPHENIRAMINE MALEATE 1 mg/5 mL; PSEUDOEPHEDRINE HYDROCHLORIDE 30 mg/5 mL
INACTIVE INGREDIENTS: SODIUM BENZOATE; ANHYDROUS CITRIC ACID; GLYCERIN; PROPYLENE GLYCOL; SORBITOL; WATER; SODIUM CITRATE; SUCRALOSE

VanaCof®

Drug Facts

Active ingredients (in each 5 mL teaspoonful)

Chlophedianol Hydrochloride 12.5 mg

Dexchlorpheniramine Maleate 1 mg

Pseudoephedrine Hydrochloride 30 mg

Purpose

Cough Suppressant

Antihistamine

Nasal Decongestant

Uses

- temporarily relieves these symptoms due to the common cold, hay fever (allergic rhinitis) or other upper respiratory allergies:
  - runny nose
  - sneezing
  - itching of the nose or throat
  - itchy, watery eyes
  - nasal congestion
  - reduces swelling of nasal passages
- cough due to minor throat and bronchial irritation

Warnings

Do not exceed recommended dosage.

Do not use this product

If you are now taking a prescription monoamine oxidase inhibitor (MAOI) (certain drugs for depression, psychiatric, or emotional conditions, or Parkinson’s disease), or for 2 weeks after stopping the MAOI drug. If you do not know if your prescription drug contains an MAOI, ask a doctor or pharmacist before taking this product

Ask a doctor before use if you have

- a cough that lasts or is chronic such as occurs with smoking, asthma or emphysema
- a cough that occurs with too much phlegm (mucus)
- a breathing problem such as emphysema or chronic bronchitis
- trouble urinating due to an enlarged prostate gland
- glaucoma
- heart disease
- high blood pressure
- thyroid disease
- diabetes

Ask a doctor before use if you are

taking sedatives or tranquilizers.

When using this product

- excitability may occur, especially in children
- may cause marked drowsiness
- alcohol, sedatives, and tranquilizers may increase the drowsiness effect
- avoid alcoholic drinks
- use caution when driving a motor vehicle or operating machinery

Stop use and ask a doctor if

- nervousness, dizziness, or sleeplessness occur
- cough or nasal congestion persists for more than 1 week, tends to recur, or is accompanied by a fever, rash or persistent headache. A persistent cough may be a sign of serious condition.
- new symptoms occur

If pregnant or breast-feeding,

ask a health professional before use.

Keep out of reach of children.

In case of overdose, get medical help or contact a Poison Control Center right away.

Directions

Do not exceed recommended dosage.

adults and children 12 years of age and over: | 2 teaspoonfuls every 6 hours, not to exceed 8 teaspoonfuls in 24 hours.
children 6 to under 12 years of age: | 1 teaspoonful every 6 hours, not to exceed 4 teaspoonfuls in 24 hours.
children under 6 years of age: | consult a doctor.

Other information

- this package is child resistant
- store at room temperature of 68°-86°F (20°-30°C) with excursions of 59°-86°F (15°-30°C)

Inactive ingredients

Citric acid anhydrous, flavor, glycerin, propylene glycol, purified water, sodium benzoate, sodium citrate dihydrate, sorbitol solution, sucralose

Questions or Comments?

Call 1-888-535-0305 9a.m. – 5p.m. CST

PRINCIPAL DISPLAY PANEL

NDC 58809-999-01
VanaCof®

Each 5 mL (1 TEASPOONFUL) CONTAINS:
Chlophedianol Hydrochloride ..... 12.5 mg
Dexchlorpheniramine Maleate ......... 1 mg
Pseudoephedrine Hydrochloride ..... 30mg